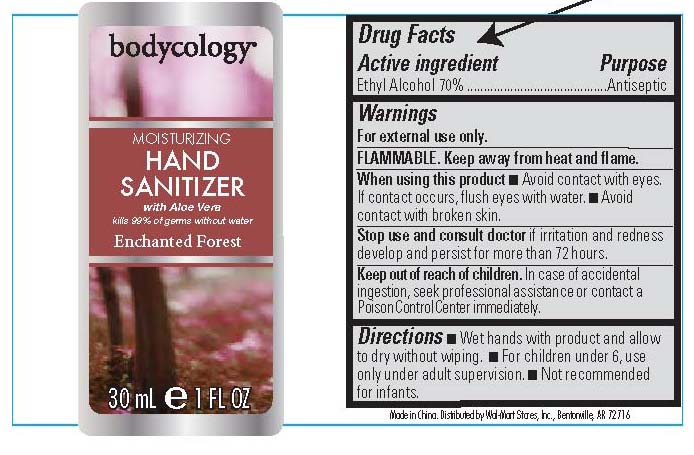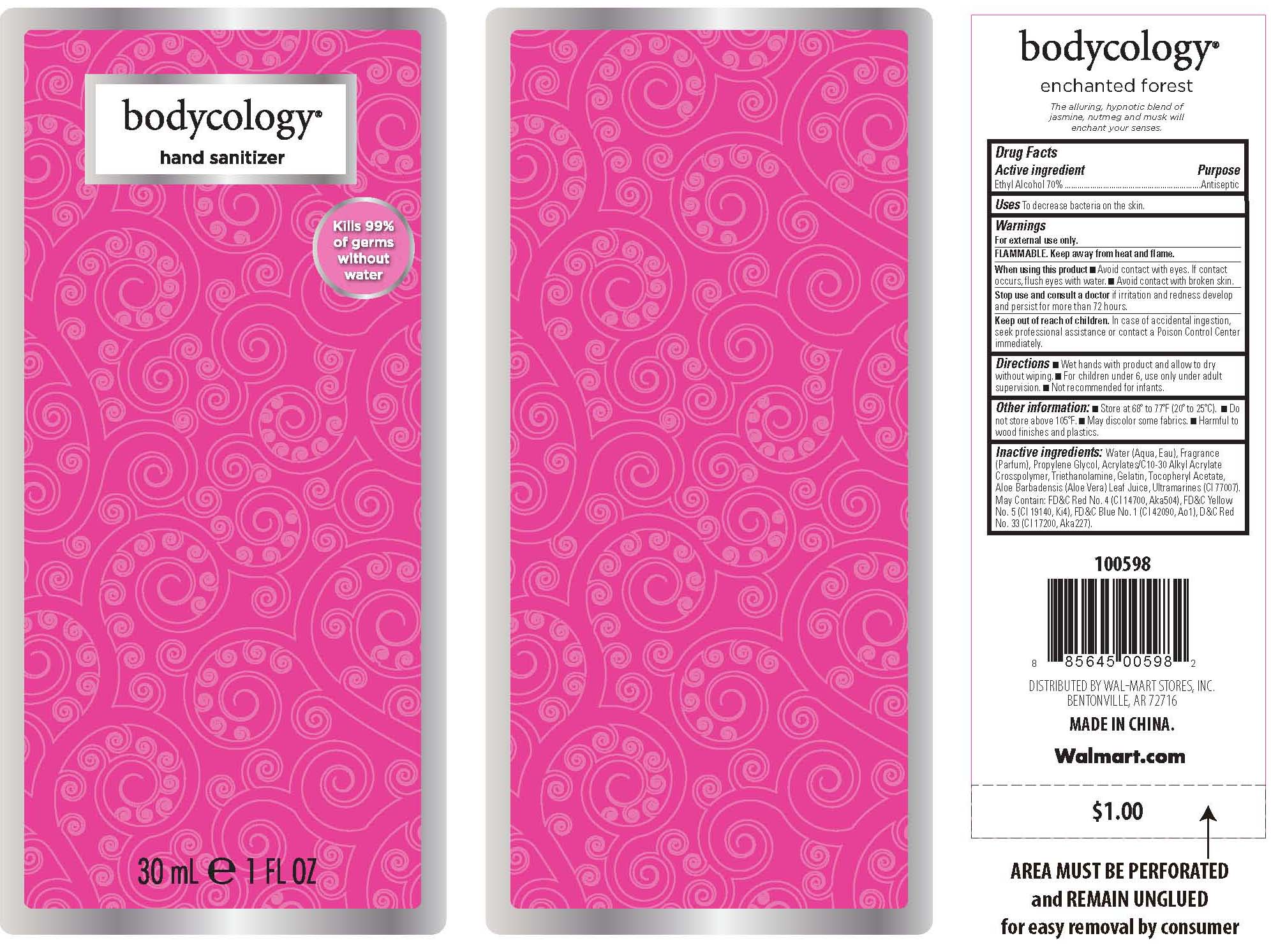 DRUG LABEL: Hand Sanitizer 
NDC: 49035-102 | Form: GEL
Manufacturer: Wal-Mart Stores, Inc
Category: otc | Type: HUMAN OTC DRUG LABEL
Date: 20110412

ACTIVE INGREDIENTS: ALCOHOL 70 mL/100 mL
INACTIVE INGREDIENTS: PROPYLENE GLYCOL; TROLAMINE; GELATIN; ALOE VERA LEAF; FD&C RED NO. 4; FD&C YELLOW NO. 5; FD&C BLUE NO. 1; D&C RED NO. 33

bodycology

Active ingredient Purpose
Ethyl Alcohol 70% ..........................................Antiseptic

PURPOSE

to decrease bacteria on the skin

Keep out of reach of children. In case of accidental ingestion,
seek professional assistance or contact a Poison Control Center
immediately.

INDICATIONS AND USAGE

For external use only

WARNINGS

FLAMMABLE. Keep away from heat and flame.
When using this product Avoid contact with eyes. If contact
occurs, flush eyes with water. Avoid contact with broken skin.
Stop use and consult a doctor if irritation and redness develop
and persist for more than 72 hours

DOSAGE AND ADMINISTRATION

Wet hands with product and allow to dry
without wiping. For children under 6, use only under adult
supervision. Not recommended for infants.

INACTIVE INGREDIENT

Water (Aqua, Eau), Fragrance
(Parfum), Propylene Glycol, Acrylates/C10-30 Alkyl Acrylate
Crosspolymer, Triethanolamine, Gelatin, Tocopheryl Acetate,
Aloe Barbadensis (Aloe Vera) Leaf Juice, Ultramarines (Cl 77007).

PACKAGE LABEL

bodycology

moisturizing hand sanitizer with aloe vera

Enchanted Forest

30mL E 1 FL OZ